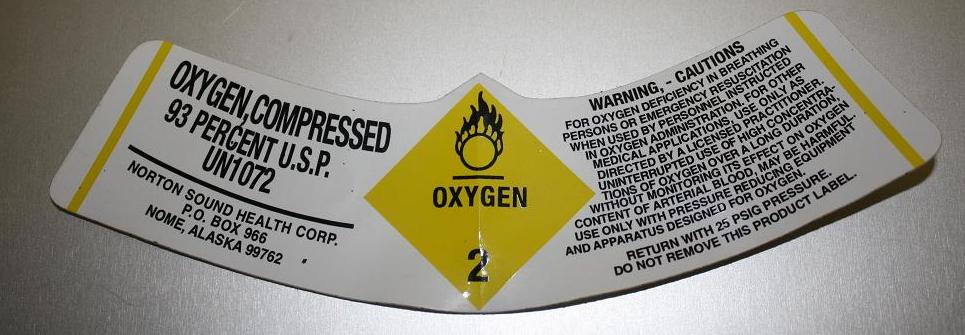 DRUG LABEL: oxygen 
NDC: 64606-100 | Form: GAS
Manufacturer: Norton Sound Health Corporation
Category: prescription | Type: HUMAN PRESCRIPTION DRUG LABEL
Date: 20110811

ACTIVE INGREDIENTS: Oxygen 93 mL/1 L

Oxygen, Compressed

PRINCIPAL DISPLAY PANEL

OXYGEN, COMPRESSED
93 PERCENT U.S.P.
UN1072
NORTON SOUND HEALTH CORP.
P.O. BOX 966
NOME, ALASKA 99762
OXYGEN 2
WARNING, - CAUTIONS
FOR OXYGEN DEFICIENCY IN BREATHING PERSONS OR EMERGENCY RESUSCITATION WHEN USED BY PERSONNEL INSTRUCTED IN OXYGEN ADMINISTRATION. FOR OTHER MEDICAL APPLICATIONS, USE ONLY AS DIRECTED BY A LICENSED PRACTITIONER. UNINTERRUPTED USE OF HIGH CONCENTRATIONS OF OXYGEN OVER A LONG DURATION WITHOUT MONITORING ITS EFFECT ON OXYGEN CONTENT OF ARTERIAL BLOOD, MAY BE HARMFUL. USE ONLY WITH PRESSURE REDUCING EQUIPMENT AND APPARATUS DESIGNED FOR OXYGEN.
RETURN WITH 25 PSIG PRESSURE.
DO NOT REMOVE THIS PRODUCT LABEL.